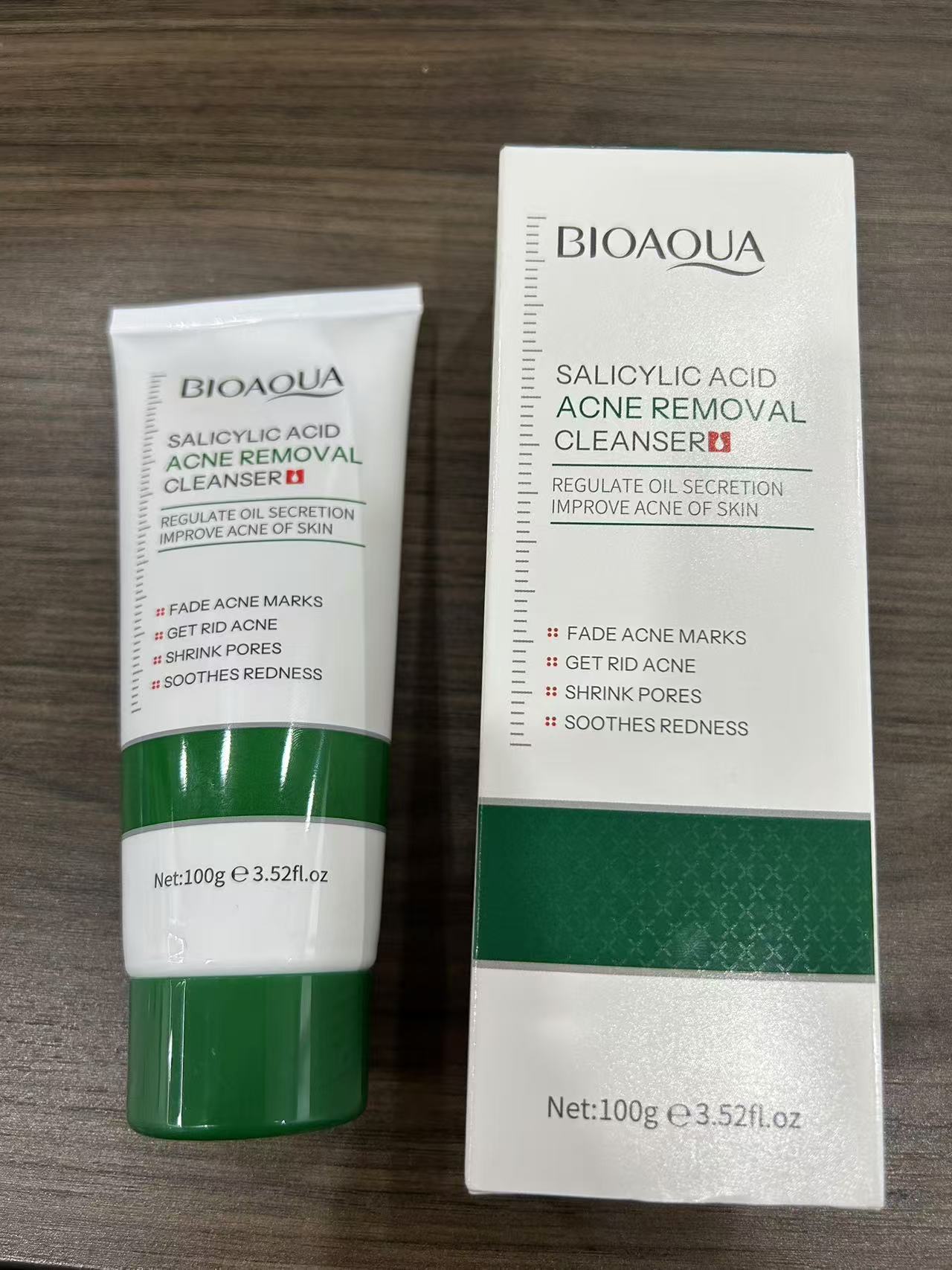 DRUG LABEL: Salicylic Acid Acne Removal Cleanser
NDC: 84766-0002 | Form: CREAM
Manufacturer: COMFMET LIMITED
Category: otc | Type: HUMAN OTC DRUG LABEL
Date: 20241012

ACTIVE INGREDIENTS: SALICYLIC ACID 2.5 g/100 g
INACTIVE INGREDIENTS: STEARIC ACID 10 g/100 g; POTASSIUM HYDROXIDE 5.5 g/100 g; BEHENYL ARACHIDATE 0.5 g/100 g; POTASSIUM CHLORIDE 3.5 g/100 g; CETEARETH-27 0.5 g/100 g; GLYCERIN 15 g/100 g; POTASSIUM COCOYL GLYCINATE 3.5 g/100 g; POTASSIUM CHLORATE 3.5 g/100 g; MYRISTIC ACID 6 g/100 g; CETEARETH-30 0.5 g/100 g; METHYLPARABEN 0.2 g/100 g; DISODIUM EDTA-COPPER 0.1 g/100 g; ACACIA SENEGAL FLOWER 2.5 g/100 g; WATER 38.912 g/100 g; DMDM HYDANTOIN 0.3 g/100 g; LAURIC ACID 4 g/100 g; PROPYLPARABEN 0.1 g/100 g; PALMITIC ACID 2 g/100 g; BUTYL METHACRYLATE/ETHYLHEXYL ACRYLATE/METHACRYLIC ACID/DIMETHYLAMINOETHYL METHACRYLATE/STYRENE/HYDROXYPROPYL METHACRYLATE COPOLYMER (60000 MW) 0.3 g/100 g; CETEARETH-33 0.5 g/100 g; FRAGRANCE 13576 0.088 g/100 g

ACTIVE INGREDIENT

Salicylic Acid 0.05%

Purpose

Acne Treatment

Uses

Treats acne - dries up acne - help prevent new acne

Warnings

For external use only.

Do not use

on the broken skin - if pregnant or lactating

When Using

avoid unnecessary sun exposure and use a sunscreen.
do not use in or near the eyes.
not that using other topical acne drugs at the same time or right after use of this product may increase dryness or skin irritation.

Stop Use

Stop useand ask a doctor if too much skin irritation or sensitivity develops or increase.

Ask Doctor

Stop useand ask a doctor if too much skin irritation or sensitivity develops or increase.

Keep Out Of Reach of children

if swallowed, get medical help or contact a Poison Control Center right away.

Directions

gently massage cleanser onto skin and remove with lukewarm water.use once daily，if bothersome dryness or peeling occurs, reduce application to every other day.

Inactive ingredients

water
glycerin
palmitidacid
stearic acid
myristic acid
potassium hydroxide
lauric acid
potassium cocoyl glycinate
ceteareth-30
behenyl alcohol
potassium chloride
ceteareth-29
hydroxypropyl methylcelulose
ceteareth-33
methylparaben
dmdm hydantoin
propylparaben
disodium edta
fragrance
acacia senegal gum

QUESTIONS

Email: commet515@gmail.com

DOSAGE AND ADMINISTRATION

use once daily，if bothersome dryness or peeling occurs, reduce application to every other day